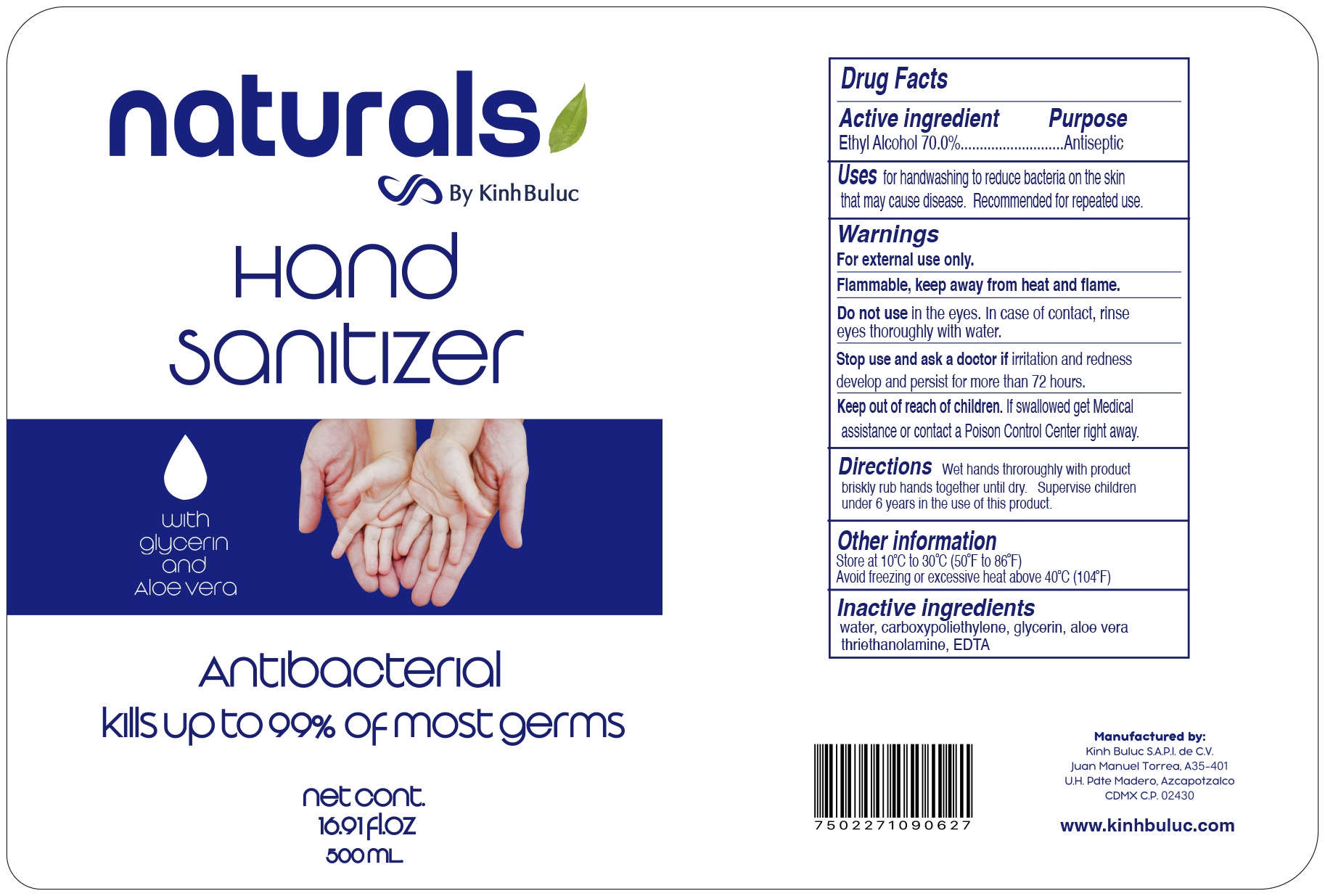 DRUG LABEL: Natural Hand Sanitizer
NDC: 79317-500 | Form: GEL
Manufacturer: Kinh Buluc, S.A.P.I. de C.V.
Category: otc | Type: HUMAN OTC DRUG LABEL
Date: 20200713

ACTIVE INGREDIENTS: ALCOHOL 0.7 mL/1 mL
INACTIVE INGREDIENTS: WATER; CARBOMER HOMOPOLYMER, UNSPECIFIED TYPE; GLYCERIN; ALOE VERA LEAF; TROLAMINE; EDETIC ACID

Natural Hand Sanitizer

Active ingredient

Ethyl Alcohol 70.0%

Purpose

Antiseptic

Uses

for handwashing to reduce bacteria on the skin that may cause disease. Recommended for repeated use.

Warnings

For external use only.

Flammable, keep away from heat and flame.

Do not use

in the eyes. In case of contact, rinse eyes thoroughly with water.

Stop use and ask a doctor if

irritation and redness develop and persist for more than 72 hours.

Keep out of reach of children.

If swallowed, get medical assistance or contact a Poison Control Center right away.

Directions

Wet hands throroughly with product briskly rub hands together until dry. Supervise children under 6 years in the use of this product.

Other information

Store at 10°C to 30°C (50°F to 86°F)

Avoid freezing or excessive heat above 40°C (104°F)

Inactive ingredients

water, carboxypoliethylene, glycerin, aloe vera, thriethanolamine, EDTA